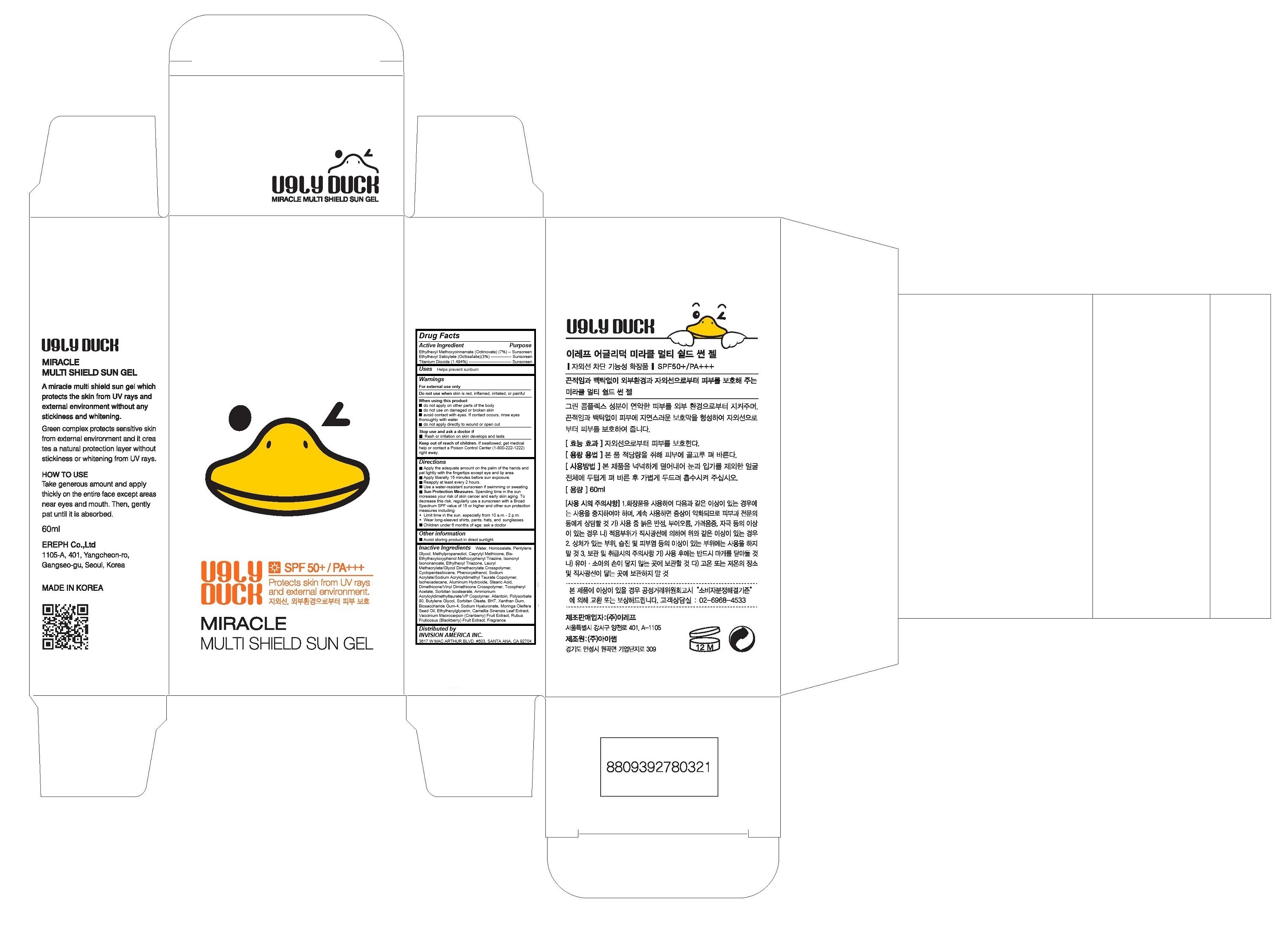 DRUG LABEL: Ugly Duck Miracle Multi Shield Sun Gel
NDC: 71624-100 | Form: GEL
Manufacturer: EREPH CO., LTD
Category: otc | Type: HUMAN OTC DRUG LABEL
Date: 20170726

ACTIVE INGREDIENTS: Octinoxate 4.2 g/60 mL; Octisalate 1.8 g/60 mL; Titanium Dioxide 0.8964 g/60 mL
INACTIVE INGREDIENTS: WATER; Homosalate; Pentylene Glycol; Methylpropanediol; CAPRYLYL TRISILOXANE; BEMOTRIZINOL; Isononyl Isononanoate; Ethylhexyl Triazone; LAURYL METHACRYLATE/GLYCOL DIMETHACRYLATE CROSSPOLYMER; CYCLOMETHICONE 5; Phenoxyethanol; SODIUM ACRYLATE/SODIUM ACRYLOYLDIMETHYLTAURATE COPOLYMER (4000000 MW); Isohexadecane; Aluminum Hydroxide; Stearic Acid; DIMETHICONE/VINYL DIMETHICONE CROSSPOLYMER (SOFT PARTICLE); .ALPHA.-TOCOPHEROL ACETATE; SORBITAN ISOSTEARATE; AMMONIUM ACRYLOYLDIMETHYLTAURATE/VP COPOLYMER; Allantoin; Polysorbate 80; Butylene Glycol; SORBITAN MONOOLEATE; TRIS-BHT MESITYLENE; Xanthan Gum; BIOSACCHARIDE GUM-4; HYALURONATE SODIUM; MORINGA OLEIFERA SEED OIL; Ethylhexylglycerin; GREEN TEA LEAF; CRANBERRY; Blackberry

Ugly Duck Miracle Multi Shield Sun Gel

Active Ingredients

Ethylhexyl Methoxycinnamate (Octinoxate) (7%)

Ethylhexyl Salicylate (Octisalate)(3%)

Titanium Dioxide (1.494%)

Purpose

Sunscreen

Keep out of reach of children

If swallowed, get medical help or contact a Poison Control Center (1-800-222-1222) right away.

Warnings

For external use only
Do not use when skin is red, inflamed, irritated, or painful
When using this product
- do not apply on other parts of the body
- do not use on damaged or broken skin
- avoid contact with eyes. If contact occurs, rinse eyes thoroughly with water
- do not apply directly to wound or open cut
Stop use and ask a doctor if
- Rash or irritation on skin develops and lasts

Uses

Helps prevent sunburn

Directions

• Apply liberally 15 minutes before sun exposure.
• Reapply at least every 2 hours.
• Use a water-resistant sunscreen if swimming or sweating.
• Sun Protection Measures. Spending time in the sun increases your risk of skin cancer and early skin aging. To decrease this risk, regularly use a sunscreen with a Broad Spectrum SPF value of 15 or higher and other sun protection measures including:
 Limit time in the sun, especially from 10 a.m. - 2 p.m.
 Wear long-sleeved shirts, pants, hats, and sunglasses.
Children under 6 months of age: ask a doctor

Inactive Ingredients

Water, Homosalate, Pentylene Glycol, Methylpropanediol, Caprylyl Methicone, Bis-Ethylhexyloxyphenol Methoxyphenyl Triazine, Isononyl Isononanoate, Ethylhexyl Triazone, Lauryl Methacrylate/Glycol Dimethacrylate Crosspolymer, Cyclopentasiloxane, Phenoxyethanol, Sodium Acrylate/Sodium Acryloyldimethyl Taurate Copolymer, Isohexadecane, Aluminum Hydroxide, Stearic Acid, Dimethicone/Vinyl Dimethicone Crosspolymer, Tocopheryl Acetate, Sorbitan Isostearate, Ammonium Acryloyldimethyltaurate/VP Copolymer, Allantoin, Polysorbate 80, Butylene Glycol, Sorbitan Oleate, BHT, Xanthan Gum, Biosaccharide Gum-4, Sodium Hyaluronate, Moringa Oleifera Seed Oil, Ethylhexylglycerin, Camellia Sinensis Leaf Extract, Vaccinium Macrocarpon (Cranberry) Fruit Extract,